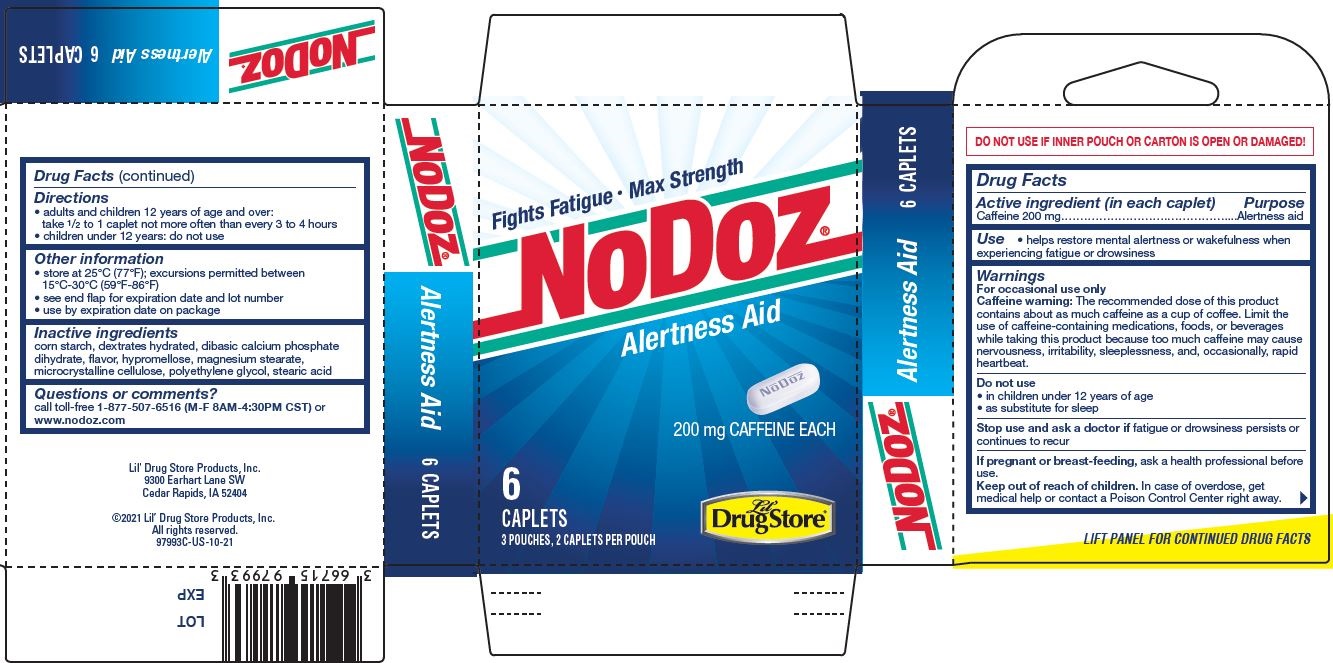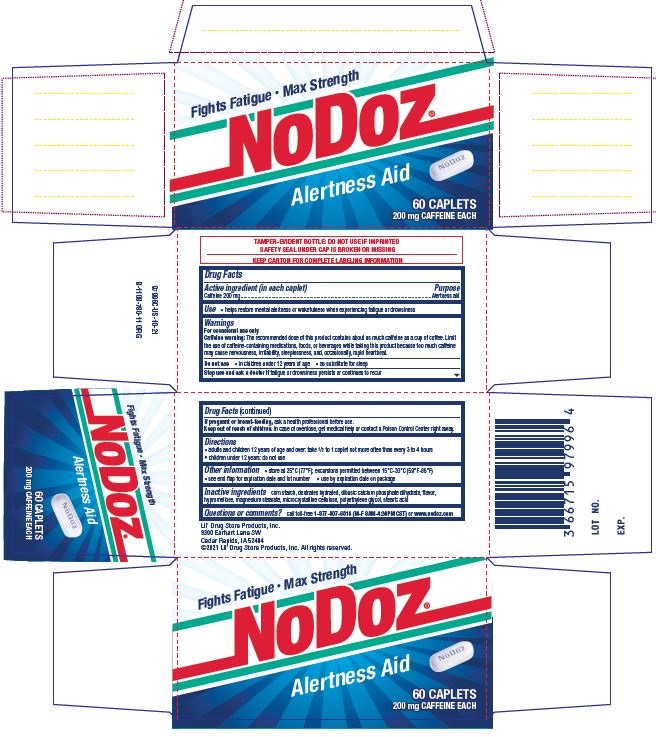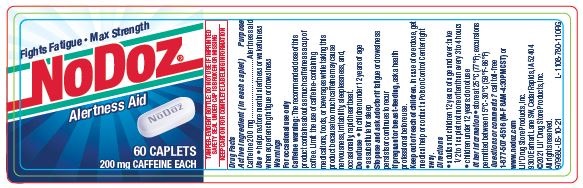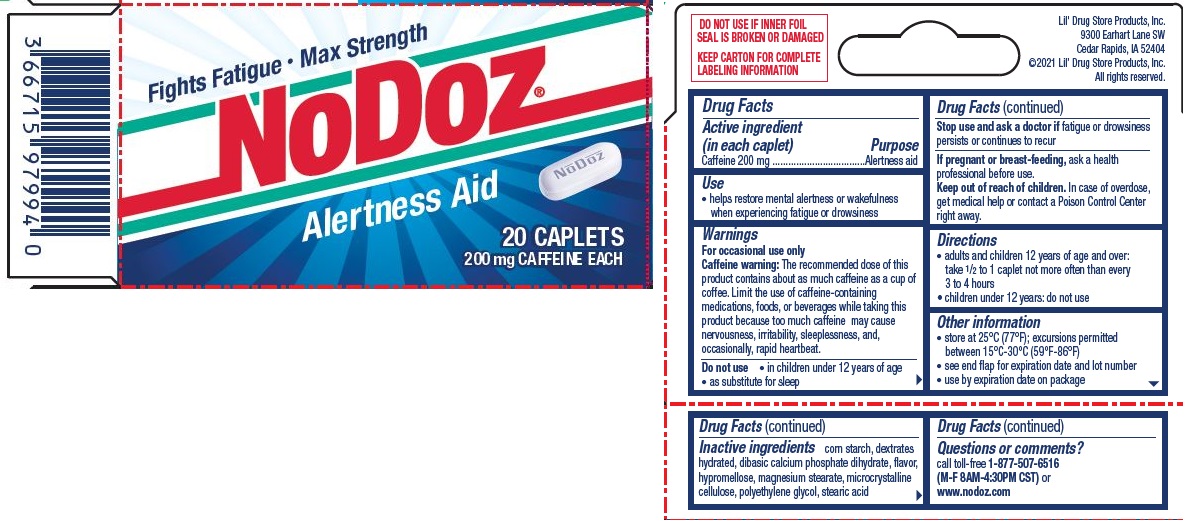 DRUG LABEL: NoDoz Alertness Aid
NDC: 66715-9899 | Form: TABLET, FILM COATED
Manufacturer: Lil' Drug Store Products, Inc.
Category: otc | Type: HUMAN OTC DRUG LABEL
Date: 20250106

ACTIVE INGREDIENTS: CAFFEINE 200 mg/1 1
INACTIVE INGREDIENTS: CALCIUM PHOSPHATE, DIBASIC, DIHYDRATE; HYPROMELLOSE, UNSPECIFIED; MAGNESIUM STEARATE; CELLULOSE, MICROCRYSTALLINE; POLYETHYLENE GLYCOL, UNSPECIFIED; STARCH, CORN; DEXTRATES; STEARIC ACID

NoDoz

Active ingredient

Active ingredient (in each caplet)

Caffeine 200 mg

Purpose

Alertness aid

Use

- helps restore mental alertness or wakefulness when experiencing fatigue or drowsiness

Warnings

For occasional use only

Caffeine warning

Caffeine warning: The recommended dose of this product contains about as much caffeine as a cup of coffee. Limit the use of caffeine-containing medications, foods, or beverages while taking this product because too much caffeine may cause nervousness, irritability, sleeplessness, and, occasionally, rapid heartbeat.

Do not use

- in children under 12 years of age
- as substitute for sleep

Stop use and ask a doctor if fatigue or drowsiness persists or continues to recur

PREGNANCY OR BREAST FEEDING

If pregnant or breast-feeding, ask a health professional before use.

Keep out of reach of children. In case of overdose, get medical help or contact a Poison Control Center right away.

Directions

- adults and children 12 years of age and over: take 1/2 to 1 caplet not more often than every 3 to 4 hours
- children under 12 years: do not use

Other information

- store at 25°C (77°F); excursions permitted between 15°C-30°C (59°F-86°F)
- see end flap for expiration date and lot number
- use by expiration date on package

Inactive ingredients

corn starch, dextrates hydrated, dibasic calcium phosphate dihydrate, flavor, hypromellose, magnesium stearate, microcrystalline cellulose, polyethylene glycol, stearic acid

Questions or comments?

call toll-free 1-877-507-6516 (M-F 8AM-4:30PM CST) or www.nodoz.com

PDP/Package 60ct

Fights Fatigue • Max Strength

NoDoz

Aler tness Aid

[caplet image]

60 CAPLETS

200 mg CAFFEINE EACH

PDP/Package 6ct

Fights Fatigue • Max Strength

NoDoz

Aler tness Aid

[caplet image]

200 mg CAFFEINE EACH

6

CAPLETS

3POUCHES, 2 CAPLETS PER POUCH

[Lil' Drug Store logo]

PDP/Package - 20 ct NDC 66715-9899-4

Fights Fatigue • Max Strength

NoDoz

Alertness Aid

[caplet image]

20 CAPLETS

200 mg CAFFEINE EACH